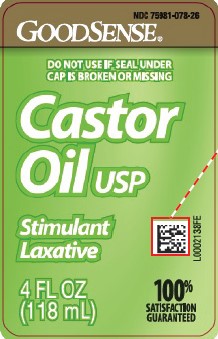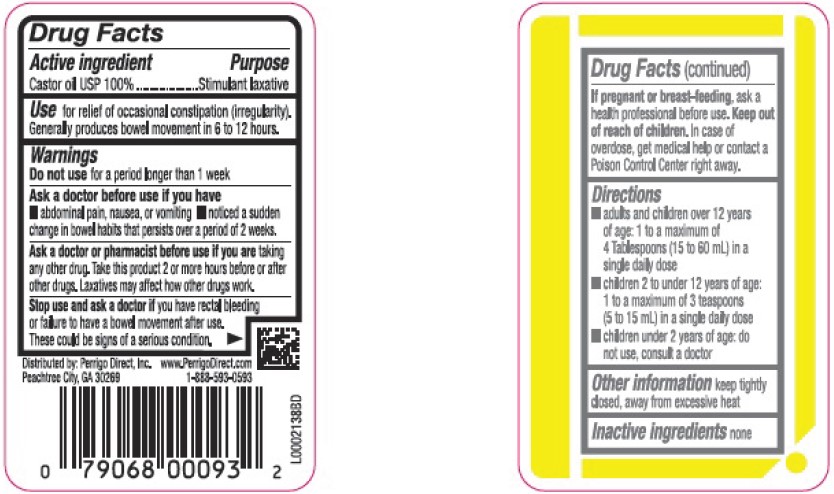 DRUG LABEL: Castor Oil
NDC: 75981-078 | Form: LIQUID
Manufacturer: Perrigo Direct, Inc
Category: otc | Type: HUMAN OTC DRUG LABEL
Date: 20260219

ACTIVE INGREDIENTS: CASTOR OIL 1000 mg/1 mL

Good Sense 078.000/078AA
Castor Oil

Active ingredient

Castor oil USP 100%

Purpose

Stimulant laxative

Use

For relief of occasional constipation (irregularity). Generally produces bowel movement in 6 to 12 hours.

Warnings

for this procduct

Do not use

For a period longer than 1 week

Ask a doctor before use if you have

- abdominal pain, nausea, or vomiting
- noticed a sudden change in bowel habits that persists over a period of 2 weeks

Ask a doctor or pharmacist before use if you are

taking any other drug. Take this product 2 or more hours before or after other drugs. Laxatives may affect how other drugs work.

Stop use and ask a doctor

If you have rectal bleeding or failure to have a bowel movement after use. These could be signs of a serious condition.

If pregnant or breast-feeding,

ask a health professional before use.

Keep out of reach of children.

In case of overdose, get medical help or contact a Poison Control Center right away.

Directions

- adults and children over 12 years of age: 1 to a maximum of 4 Tablespoons (15 to 60 mL) in a single daily dose
- children 2 to under 12 years of age: 1 to a maximum of 3 teaspoons (5 to 15 mL) in a single daily dose
- children under 2 years of age: do not use, consult a doctor

Other Information

keep tightly closed, away from excessive heat

Invactive Ingredient

None

Adverse reaction

Distributed by: Perrigo Direct, Inc,

Peachtree City, GA 30269

www.PerrigoDirect.com

1-888-593-0593

Principal display panel

NDC 75981-078-26

GoodSense®

DO NOT USE IF SEAL UNDER CAP IS BROKEN OR MISSING

Castor Oil USP

Stimulant laxative

100% SATISFACTION GUARANTEED

4 FL OZ (118 mL)